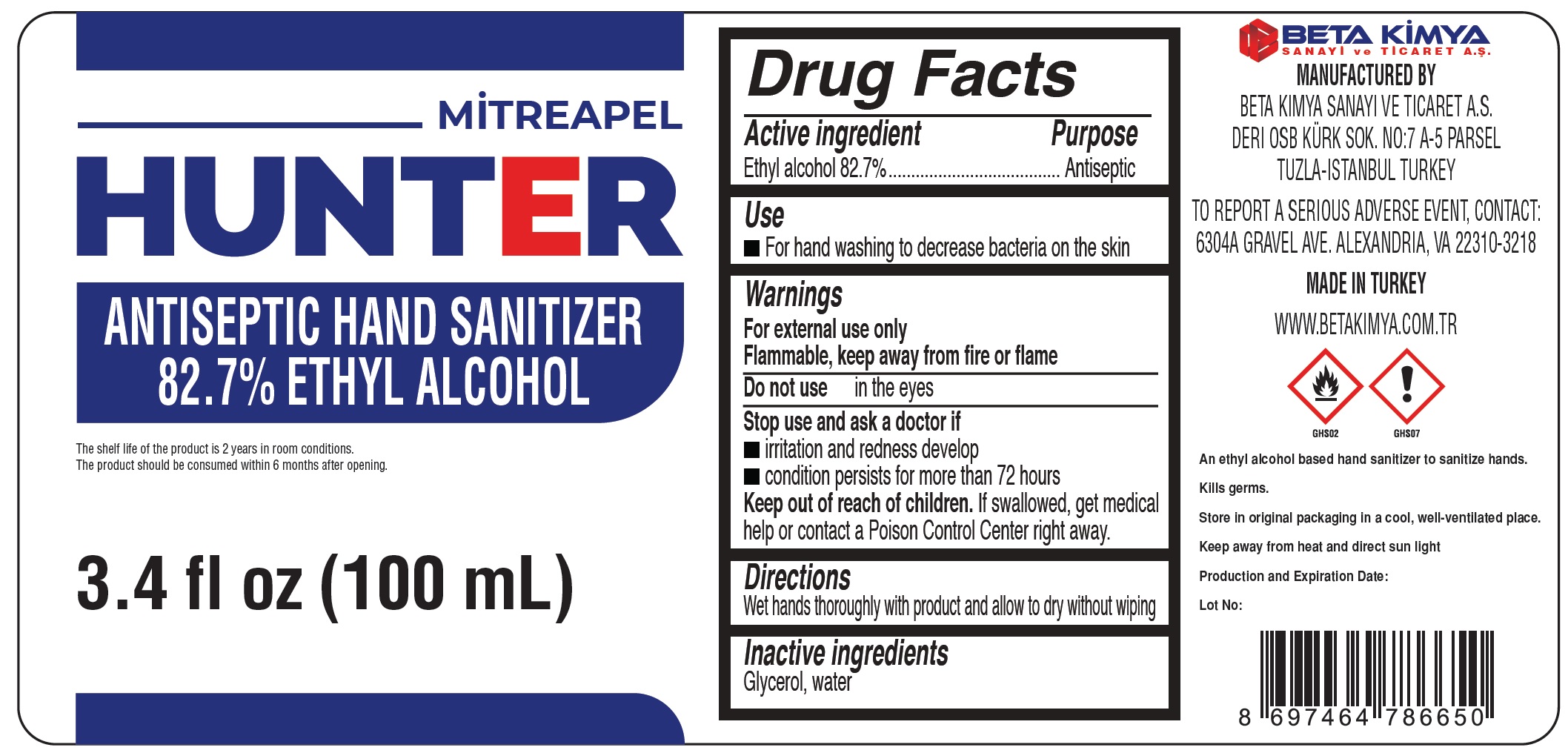 DRUG LABEL: Mitreapel Hunter Antiseptic Hand Sanitizer
NDC: 79932-000 | Form: LIQUID
Manufacturer: BETA KIMYA SANAYI VE TICARET ANONIM SIRKETI
Category: otc | Type: HUMAN OTC DRUG LABEL
Date: 20211008

ACTIVE INGREDIENTS: ALCOHOL 0.827 mL/1 mL
INACTIVE INGREDIENTS: GLYCERIN; WATER

Mitreapel Hunter Antiseptic Hand Sanitizer

Active ingredient

Ethyl alcohol 82.7%

Purpose

Antiseptic

Use

- For hand washing to decrease bacteria on the skin

Warnings

For external use only
Flammable, keep away from fire or flame

Do not use

in the eyes

Stop use and ask a doctor if

- irritation and redness develop
- condition persists for more than 72 hours

Keep out of reach of children.

If swallowed, get medical help or contact a Poison Control Center right away.

Directions

Wet hands thoroughly with product and allow to dry without wiping

Inactive ingredients

Glycerol, water